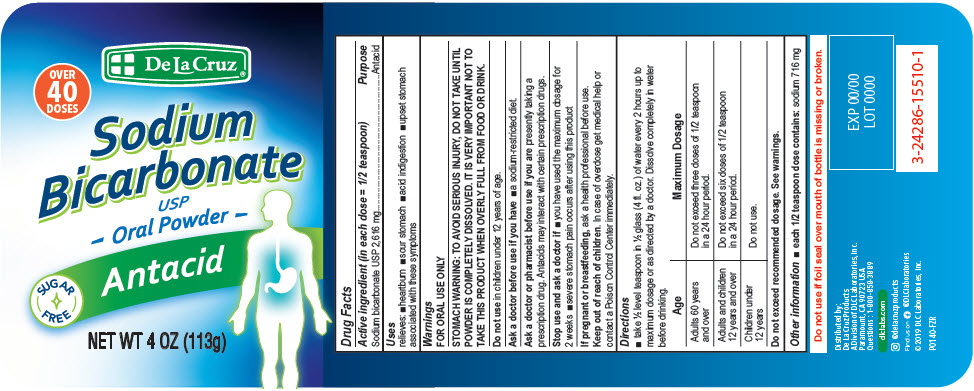 DRUG LABEL: DE LA CRUZ SODIUM BICARBONATE ANTACID
NDC: 24286-1537 | Form: POWDER
Manufacturer: DLC Laboratories, Inc.
Category: otc | Type: HUMAN OTC DRUG LABEL
Date: 20260107

ACTIVE INGREDIENTS: SODIUM BICARBONATE 2.6 g/2.6 g

DE LA CRUZ® SODIUM BICARBONATE ANTACID

Drug Facts

Active ingredient (in each dose = 1/2 teaspoon)

Sodium bicarbonate USP 2,616 mg

Purpose

Antacid

Uses

relieves:

- heartburn
- sour stomach
- acid indigestion
- upset stomach associated with these symptoms

Warnings

FOR ORAL USE ONLY

STOMACH WARNING

TO AVOID SERIOUS INJURY, DO NOT TAKE UNTIL POWDER IS COMPLETELY DISSOLVED. IT IS VERY IMPORTANT NOT TO TAKE THIS PRODUCT WHEN OVERLY FULL FROM FOOD OR DRINK.

Do not use in children under 12 years of age.

Ask a doctor before use if you have

- a sodium-restricted diet.

Ask a doctor or pharmacist before use if you are presently taking a prescription drug. Antacids may interact with certain prescription drugs.

Stop use and ask a doctor if

- you have used the maximum dosage for 2 weeks
- severe stomach pain occurs after using this product

PREGNANCY OR BREAST FEEDING

If pregnant or breastfeeding, ask a health professional before use.

Keep out of reach of children. In case of overdose get medical help or contact a Poison Control Center immediately.

Directions

- take ½ level teaspoon in ½ glass (4 fl. oz.) of water every 2 hours up to maximum dosage or as directed by a doctor. Dissolve completely in water before drinking.

Age | Maximum Dosage
Adults 60 years and over | Do not exceed three doses of 1/2 teaspoon in a 24 hour period.
Adults and children 12 years and over | Do not exceed six doses of 1/2 teaspoon in a 24 hour period.
Children under 12 years | Do not use.

Do not exceed recommended dosage. See warnings.

Other information

- each 1/2 teaspoon dose contains: sodium 716 mg

Distributed by:
De La Cruz Products
A Division of DLC Laboratories, Inc.
Paramount, CA 90723 USA

Questions

1-800-858-3889

Inactive Ingredient

none

PRINCIPAL DISPLAY PANEL - 113 g Bottle Label

De La Cruz®

OVER
40
DOSES

Sodium
Bicarbonate

USP
- Oral Powder -

SUGAR
FREE

Antacid

NET WT 4 OZ (113g)